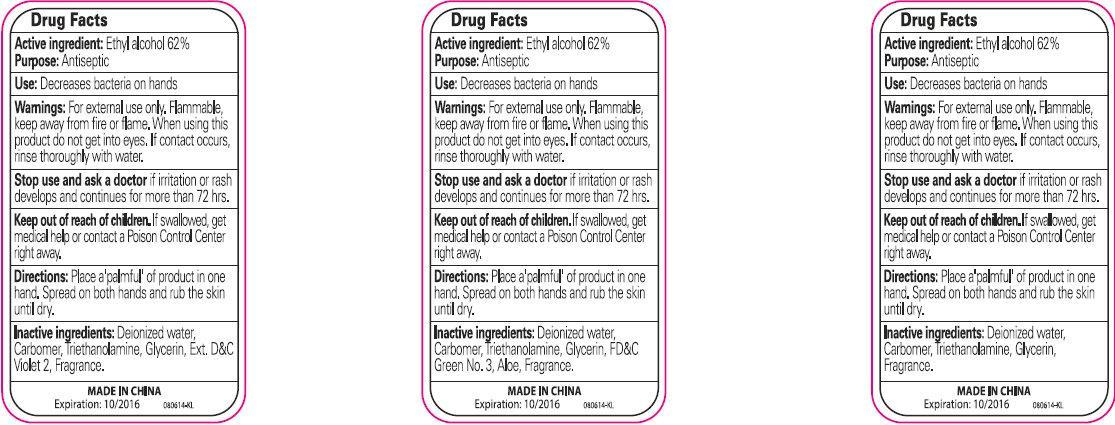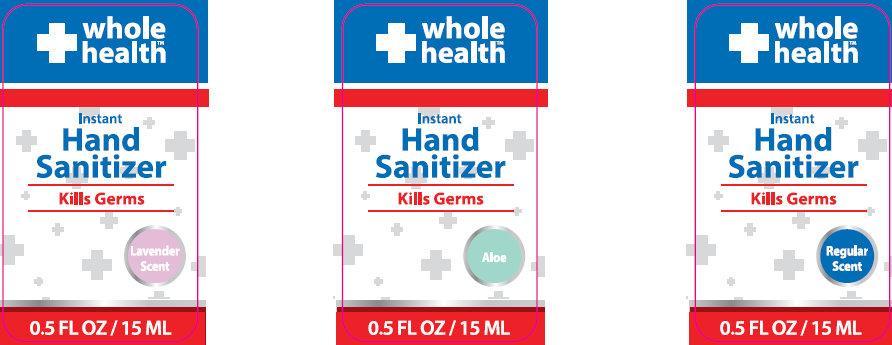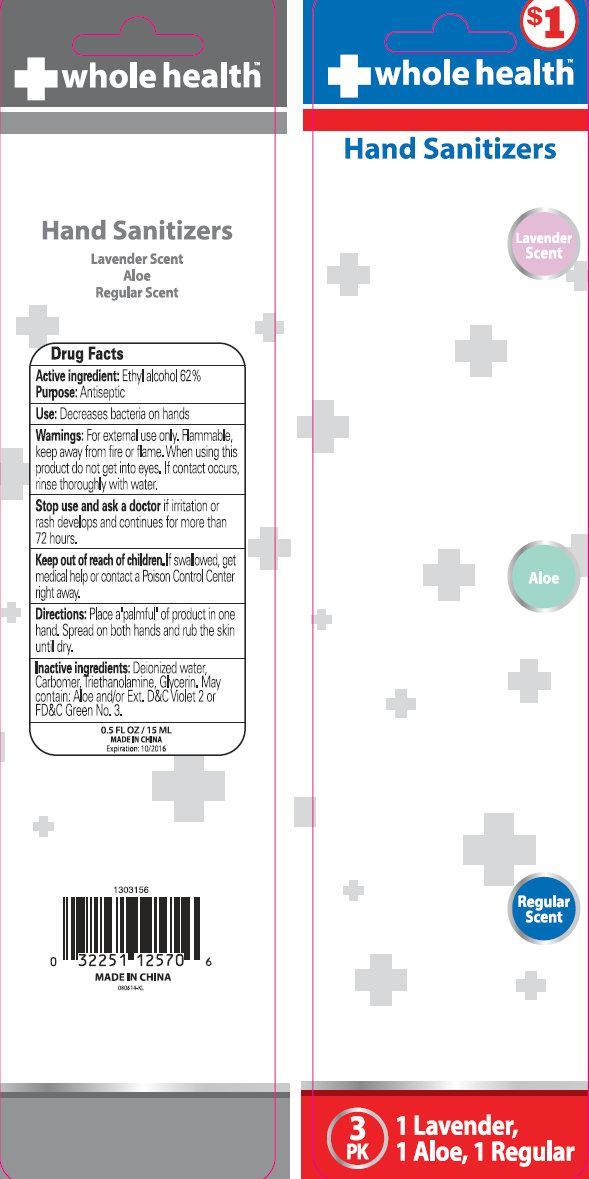 DRUG LABEL: whole health Hand Sanitizers
NDC: 69222-000 | Form: KIT | Route: TOPICAL
Manufacturer: Suzhou Jingying Daily Necessities Co., Ltd.
Category: otc | Type: HUMAN OTC DRUG LABEL
Date: 20140917

ACTIVE INGREDIENTS: ALCOHOL 62 mL/100 mL; ALCOHOL 62 mL/100 mL; ALCOHOL 62 mL/100 mL
INACTIVE INGREDIENTS: WATER; TROLAMINE; GLYCERIN; D&C VIOLET NO. 2; WATER; TROLAMINE; GLYCERIN; FD&C GREEN NO. 3; ALOE; WATER; TROLAMINE; GLYCERIN

whole health Hand Sanitizers Kit

Active Ingredient

Ethyl Alcohol 62%

Purpose

Antiseptic

Uses

Decreases bacteria on hands.

Warnings

For external use only. Flammable, keep away from fire or flame.

When using this product

do not get into eyes. If contact occurs, rinse thoroughly with water.

Stop use and ask a doctor

if irritation or rash develops and continues for more than 72 hours.

Keep out of reach of children.

If swallowed, get medical help or contact a Poison Control Center right away.

Directions

Place a palmful of product in one hand. Spread on both hands and rub the skin until dry.

Inactive Ingredients

Deionized water, Carbomer, Triethanolamine, Glycerin, D&C Violet 2, Fragrance

PACKAGE LABEL

0.5FLOZ/15 ML

MADE IN CHINA

Expiration: 10/2016

Active Ingredient

Ethyl Alcohol 62%

Purpose

Antiseptic

Uses

Decreases bacteria on hands.

Warnings

For external use only. Flammable, keep away from fire or flame.

When using this product

do not get into eyes. If contact occurs, rinse thoroughly with water.

Stop use and ask a doctor

if irritation or rash develops and continues for more than 72 hours.

Keep out of reach of children.

If swallowed, get medical help or contact a Poison Control Center right away.

Directions

Place a palmful of product in one hand. Spread on both hands and rub the skin until dry.

Inactive Ingredients

Deionized water, Carbomer, Triethanolamine, Glycerin, FD&C Green No. 3, Aloe, Fragrance.

MADE IN CHINA

Expiration: 10/2016

Active Ingredient

Ethyl Alcohol 62%

Purpose

Antiseptic

Uses

Decreases bacteria on hands.

Warnings

For external use only. Flammable, keep away from fire or flame.

When using this product

do not get into eyes. If contact occurs, rinse thoroughly with water.

Stop use and ask a doctor

if irritation or rash develops and continues for more than 72 hours.

Keep out of reach of children.

If swallowed, get medical help or contact a Poison Control Center right away.

Directions

Place a palmful of product in one hand. Spread on both hands and rub the skin until dry.

Inactive Ingredients

Deionized water, Carbomer, Triethanolamine, Glycerin, Fragrance

PACKAGE LABEL

whole health

Instant
Hand Sanitizer

Kills Germs

Lavender Scent

0.5 FL OZ/15ML

PACKAGE LABEL

whole health

Instant Hand Sanitizer

Kills Germs

Aloe

0.5 FL OZ/15ML

PACKAGE LABEL

whole health

Instant Hand Sanitizer

Kills Germs

Regular Scent

0.5 FL OZ/15ML